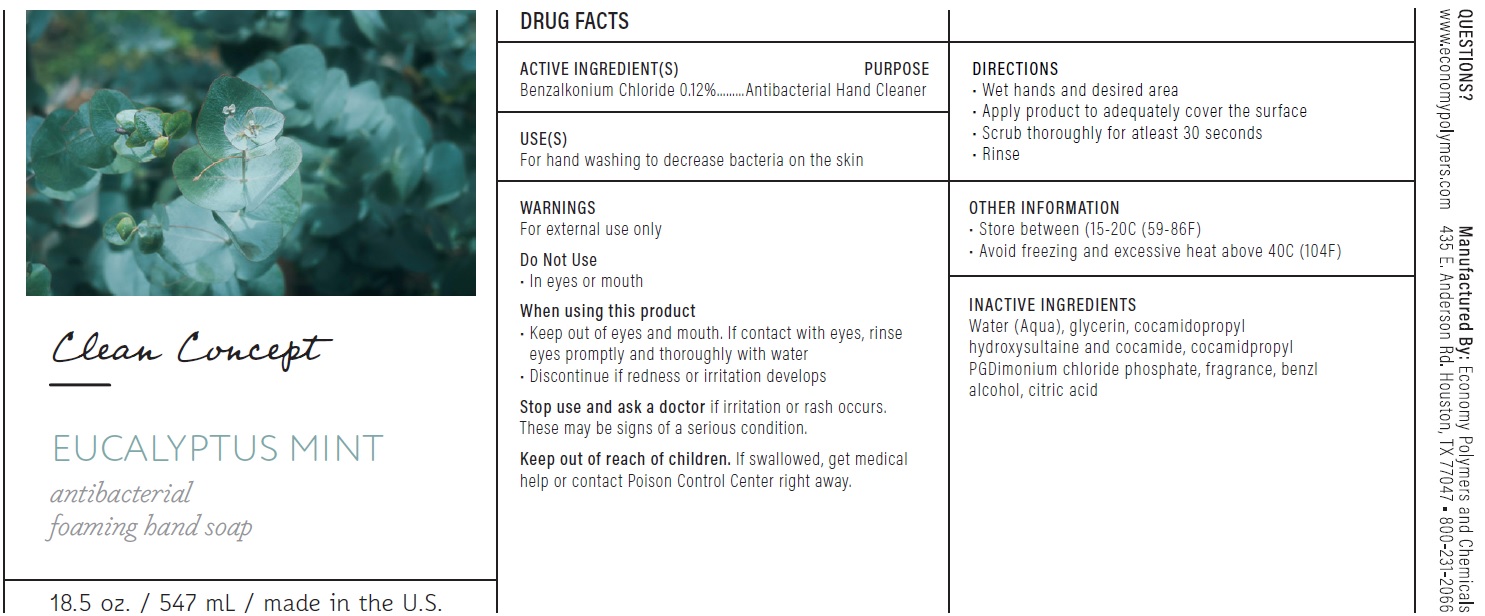 DRUG LABEL: Clean Concept Eucalyptus Mint Antibacterial Foaming Hand
NDC: 74830-545 | Form: LIQUID
Manufacturer: Economy Polymers and Chemicals
Category: otc | Type: HUMAN OTC DRUG LABEL
Date: 20201125

ACTIVE INGREDIENTS: BENZALKONIUM CHLORIDE 1.2 mg/1 mL
INACTIVE INGREDIENTS: WATER; GLYCERIN; COCAMIDOPROPYL HYDROXYSULTAINE; COCAMIDE; COCAMIDOPROPYL PROPYLENE GLYCOL-DIMONIUM CHLORIDE PHOSPHATE; BENZYL ALCOHOL; CITRIC ACID MONOHYDRATE

Clean Concept Eucalyptus Mint Antibacterial Foaming Hand Soap

ACTIVE INGREDIENT(S)

Benzalkonium Chloride 0.12%

PURPOSE

Antibacterial Hand Cleaner

USE(S)

For hand washing to decrease bacteria on the skin

WARNINGS

For external use only

Do Not Use

• In eyes or mouth

When using this product

• Keep out of eyes and mouth. If contact with eyes, rinse eyes promptly and thoroughly with water
• Discontinue if redness or irritation develops

Stop use and ask a doctor

if irritation or rash occurs. These may be signs of a serious condition.

Keep out of reach of children.

If swallowed, get medical help or contact Poison Control Center right away.

DIRECTIONS

• Wet hands and desired area
• Apply product to adequately cover the surface
• Scrub thoroughly for atleast 30 seconds
• Rinse

OTHER INFORMATION

• Store between (15-20C (59-86F)
• Avoid freezing and excessive heat above 40C (104F)

INACTIVE INGREDIENTS

Water (Aqua), glycerin, cocamidopropyl hydroxysultaine and cocamide, cocamidpropyl PGDimonium chloride phosphate, fragrance, benzl alcohol, citric acid